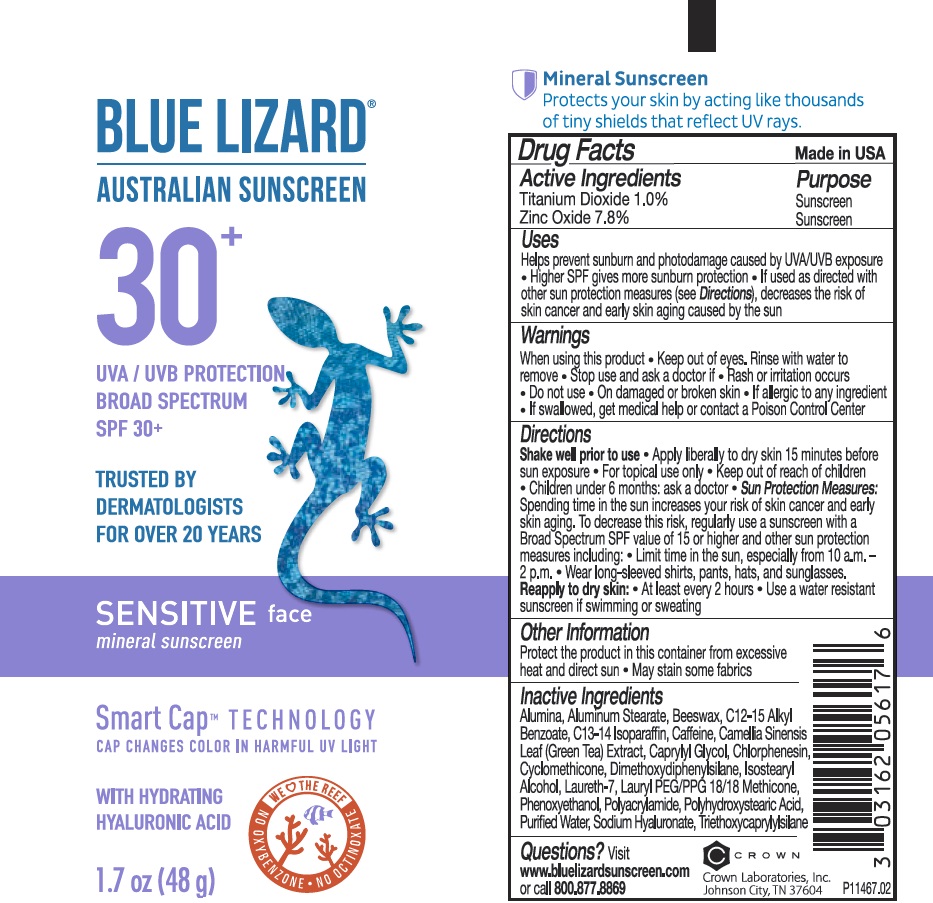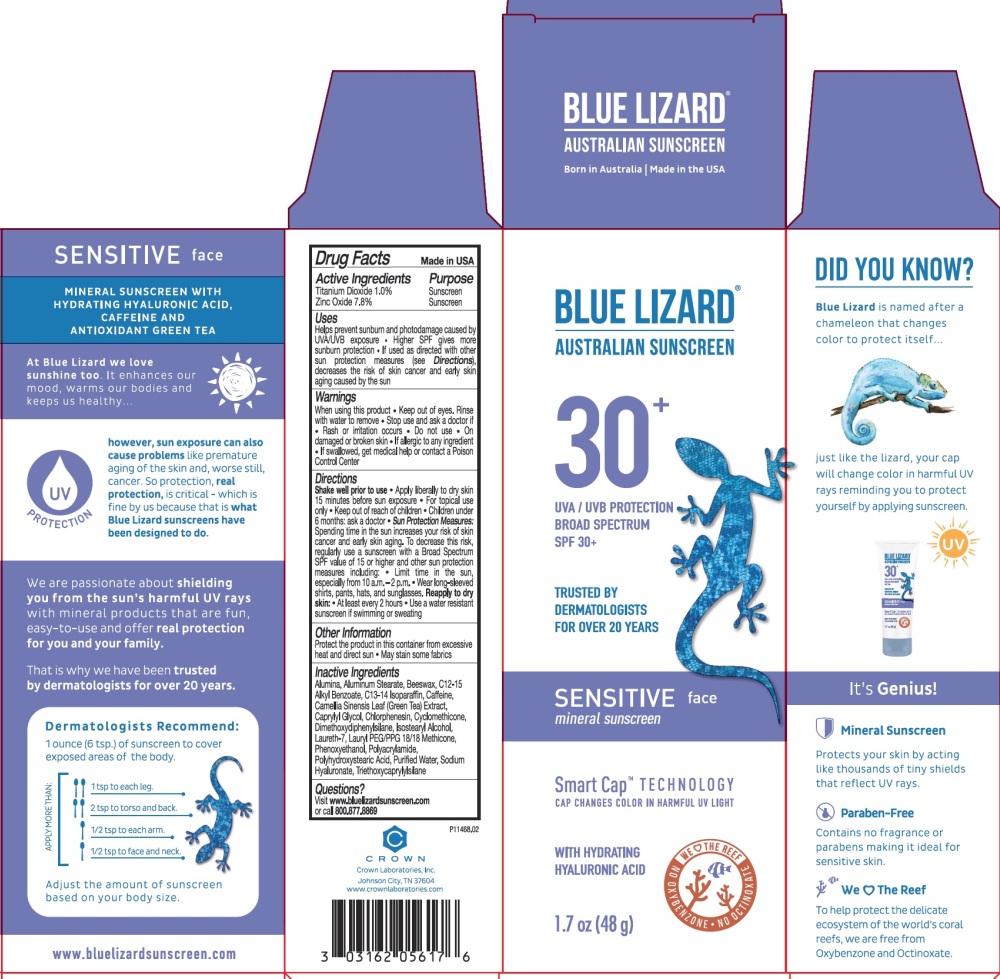 DRUG LABEL: Blue Lizard Sensitive Face Sunscreen
NDC: 0316-2056 | Form: GEL
Manufacturer: Crown Laboratories
Category: otc | Type: HUMAN OTC DRUG LABEL
Date: 20260112

ACTIVE INGREDIENTS: ZINC OXIDE 83.4 mg/1 g; TITANIUM DIOXIDE 10 mg/1 g
INACTIVE INGREDIENTS: WATER; ALKYL (C12-15) BENZOATE; CYCLOMETHICONE; C13-14 ISOPARAFFIN; LAURETH-7; GREEN TEA LEAF; YELLOW WAX; CAFFEINE; PHENOXYETHANOL; CAPRYLYL GLYCOL; CHLORPHENESIN; LAURYL PEG/PPG-18/18 METHICONE; ALUMINUM OXIDE; HYALURONATE SODIUM; TRIETHOXYCAPRYLYLSILANE; ISOSTEARYL ALCOHOL; ALUMINUM STEARATE; POLYACRYLAMIDE (1500 MW); DIMETHOXYDIPHENYLSILANE; POLYHYDROXYSTEARIC ACID (2300 MW)

Blue Lizard Sensitive Face Sunscreen

Active Ingredients

Titanium Dioxide 1.0%

Zinc Oxide 7.8%

Purpose

Sunscreen

Uses

- Helps prevent sunburn and photodamage caused by UVA/UVB exposure
- Higher SPF gives more sunburn protection
- If used as directed with other sun protection measures (see Directions), decreases the risk of skin cancer and early skin aging caused by the sun

Warnings

- When using this product
- Keep out of eyes. Rinse with water to remove
- Stop use and ask a doctor if
- Rash or irritation occurs
- Do not use
- On damaged or broken skin
- If allergic to any ingredient
- If swallowed, get medical help or contact a Poison Control Center

Directions

- Shake well prior to use
- Apply liberally to dry skin 15 minutes before sun exposure
- For topical use only
- Children under 6 months: ask a doctor
- Sun Protection Measures: Spending time in the sun increases your risk of skin cancer and early skin aging. To decrease this risk, regularly use a sunscreen with a Broad Spectrum SPF value of 15 or higher and other sun protection measures including:
- Limit time in the sun, especially from 10 a.m. - 2 p.m.
- Wear long-sleeved shirts, pants, hats, and sunglasses.
- Reapply to dry skin:
- At least every 2 hours
- Use a water resistant sunscreen if swimming or sweating

Other Information

- Protect the product in this container from excessive heat and direct sun
- May stain some fabrics

Inactive Ingredients

Alumina, Aluminum Stearate, Beeswax, C12-15 Alkyl Benzoate, C13-14 Isoparaffin, Caffeine, Camellia Sinensis Leaf (Green Tea) Extract, Caprylyl Glycol, Chlorphenesin, Cyclomethicone, Dimethoxydiphenylsilane, Isostearyl Alcohol, Laureth-7, Lauryl PEG/PPG 18/18 Methicone, Phenoxyethanol, Polyacrylamide, Polyhydroxystearic Acid, Purified Water, Sodium Hyaluronate, Triethoxycaprylylsilane

Questions?

Visit www.bluelizardsunscreen.com or call 800.877.8869

Crown Laboratories, Inc., Johnson City, TN 37604

Blue Lizard Sensitive Face Tube

BLUE LIZARD

AUSTRALIAN SUNSCREEN

30+

UVA/UVB PROTECTION

BROAD SPECTRUM

SPF 30+

TRUSTED BY DERMATOLOGISTS FOR OVER 20 YEARS

SENSITIVE face

mineral sunscreen

Smart Cap TECHNOLOGY

CAP CHANGES COLOR IN HARMFUL UV LIGHT

WITH HYDRATING HYALURONIC ACID

Mineral Sunscreen

Protects your skin by acting like thousands of tiny shields that reflect UV rays.

P11467.02

Blue Lizard Sensitive Face Carton

P11468.02